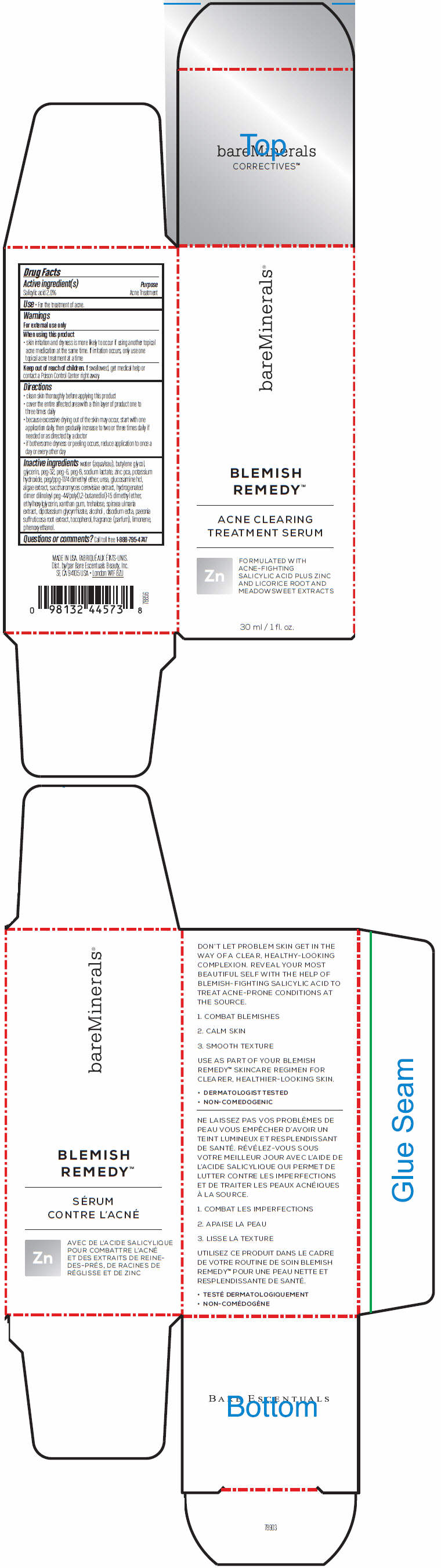 DRUG LABEL: bareMinerals Blemish Remedy Acne Clearing Treatment Serum
NDC: 98132-771 | Form: EMULSION
Manufacturer: Bare Escentuals Beauty, Inc.
Category: otc | Type: HUMAN OTC DRUG LABEL
Date: 20160512

ACTIVE INGREDIENTS: SALICYLIC ACID 20 mg/1 mL
INACTIVE INGREDIENTS: WATER; BUTYLENE GLYCOL; GLYCERIN; POLYETHYLENE GLYCOL 1500; POLYETHYLENE GLYCOL 300; POLYETHYLENE GLYCOL 400; SODIUM LACTATE; ZINC PIDOLATE; POTASSIUM HYDROXIDE; PEG/PPG-17/4 DIMETHYL ETHER; UREA; GLUCOSAMINE HYDROCHLORIDE; SACCHAROMYCES CEREVISIAE; ETHYLHEXYLGLYCERIN; XANTHAN GUM; TREHALOSE; GLYCYRRHIZINATE DIPOTASSIUM; ALCOHOL; EDETATE DISODIUM; PAEONIA SUFFRUTICOSA ROOT; TOCOPHEROL; LIMONENE, (+/-)-; PHENOXYETHANOL

bareMinerals® Blemish Remedy™ Acne Clearing Treatment Serum

Drug Facts

Active ingredient(s)

Salicylic acid 2.0%

Purpose

Acne Treatment

Use

- For the treatment of acne.

Warnings

For external use only

When using this product:

- skin irritation and dryness is more likely to occur if using another topical acne medication at the same time. If irritation occurs, only use one topical acne treatment at a time

Keep out of reach of children. If swallowed, get medical help or contact a Poison Control Center right away.

Directions

- clean skin thoroughly before applying this product
- cover the entire affected area with a thin layer of product one to three times daily
- because excessive drying out of the skin may occur, start with one application daily, then gradually increase to two or three times daily if needed or as directed by a doctor
- if bothersome dryness or peeling occurs, reduce application to once a day or every other day

Inactive ingredients

water (aqua/eau), butylene glycol, glycerin, peg-32, peg-6, peg-8, sodium lactate, zinc pca, potassium hydroxide, peg/ppg-17/4 dimethyl ether, urea, glucosamine hcl, algae extract, saccharomyces cerevisiae extract, hydrogenated dimer dilinoleyl peg-44/poly(1,2-butanediol)-15 dimethyl ether, ethylhexylglycerin, xanthan gum, trehalose, spiraea ulmaria extract, dipotassium glycyrrhizate, alcohol , disodium edta, paeonia suffruticosa root extract, tocopherol, fragrance (parfum), limonene, phenoxyethanol.

Questions or comments?

Call toll free 1-888-795-4747

Dist. by Bare Escentuals Beauty, Inc.
SF, CA 94105 USA

PRINCIPAL DISPLAY PANEL - 30 ml Bottle Carton

bareMinerals®

BLEMISH
REMEDY™

ACNE CLEARING
TREATMENT SERUM

Zn

FORMULATED WITH
ACNE-FIGHTING
SALICYLIC ACID PLUS ZINC
AND LICORICE ROOT AND
MEADOWSWEET EXTRACTS

30 ml / 1 fl. oz.